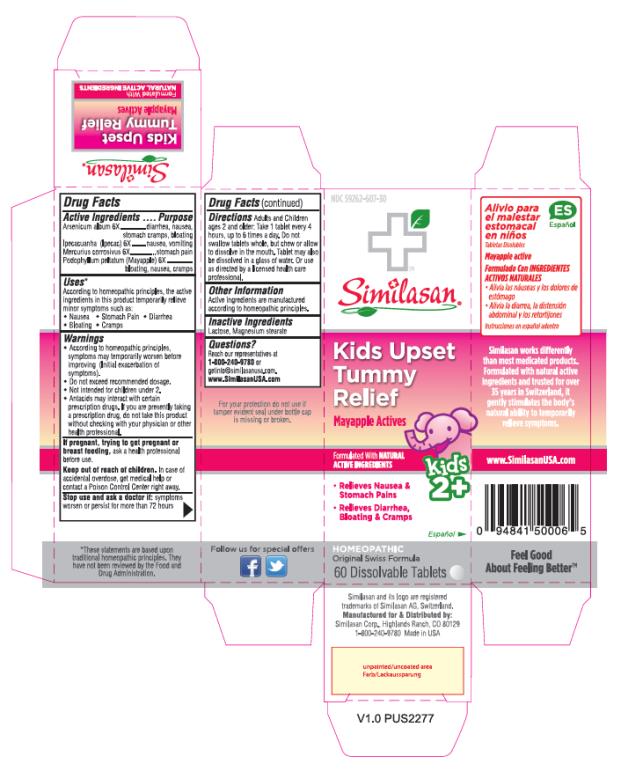 DRUG LABEL: Kids Upset Tummy Relief
NDC: 59262-607 | Form: TABLET, ORALLY DISINTEGRATING
Manufacturer: Similasan Corporation
Category: homeopathic | Type: HUMAN OTC DRUG LABEL
Date: 20161212

ACTIVE INGREDIENTS: ARSENIC TRIOXIDE 6 [hp_X]/1 1; IPECAC 6 [hp_X]/1 1; MERCURIC CHLORIDE 6 [hp_X]/1 1; PODOPHYLLUM 6 [hp_X]/1 1
INACTIVE INGREDIENTS: LACTOSE; MAGNESIUM STEARATE

Kids Upset Tummy Relief

Kids Upset Tummy Relief

Drug Facts

Active Ingredients

Arsenicum album 6X

Purpose

diarrhea, nausea, stomach cramps, bloating

Active Ingredients

Ipecacuanha (Ipecac) 6X

Purpose

nausea, vomiting

Active Ingredients

Mercurius corrosivus 6X

Purpose

stomach pain

Active Ingredients

Podophyllum peltatum (Mayapple) 6X

Purpose

bloating, nausea, cramps

Uses*

According to homeopathic principles, the active ingredients in this product temporarily relieve minor symptoms such as:
• Nausea
• Stomach Pain
• Diarrhea
• Bloating
• Cramps

Warnings

• According to homeopathic principles, symptoms may temporarily worsen before improving (Initial exacerbation of symptoms).

• Do not exceed recommended dosage.

• Not intended for children under 2.

• Antacids may interact with certain prescription drugs. If you are presently taking a prescription drug, do not take this product without checking with your physician or other health professional.

Keep out of reach of children.

In case of accidental overdose, get medical help or contact a Poison Control Center right away.

Stop use and ask a doctor if:

symptoms worsen or persist for more than 72 hours

Directions Adults and Children ages 2 and older:

Take 1 tablet every 4 hours, up to 6 times a day. Do not swallow tablets whole, but chew or allow to dissolve in the mouth. Tablet may also be dissolved in a glass of water. Or use as directed by a licensed health care professional.

Other Information

Active ingredients are manufactured according to homeopathic principles.

Inactive Ingredients

Lactose, Magnesium stearate

Questions?

Reach our representatives at 1-800-240-9780 or getinfo@similasanusa.com. www.SimilasanUSA.com

*These statements are based upon traditional homeopathic principles. They have not been reviewed by the Food and Drug Administration.

PRINCIPAL DISPLAY PANEL

NDC 59262-607-30
Similasan
Kids Upset
Tummy
Relief
Mayapple Actives
60 Dissolvable Tablets